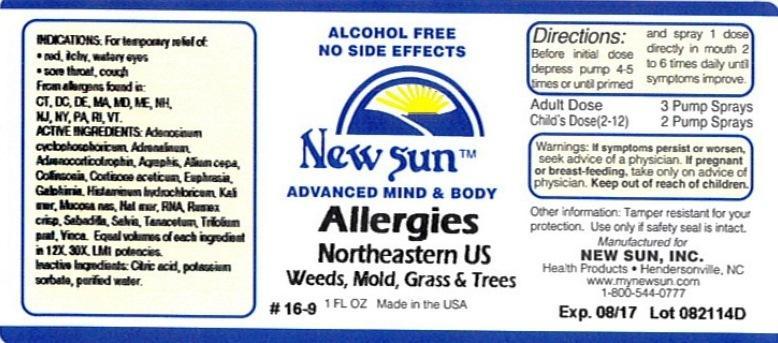 DRUG LABEL: Allergies Northeastern US
NDC: 66579-0037 | Form: LIQUID
Manufacturer: New Sun Inc.
Category: homeopathic | Type: HUMAN OTC DRUG LABEL
Date: 20141024

ACTIVE INGREDIENTS: ADENOSINE CYCLIC PHOSPHATE 12 [hp_X]/29 mL; EPINEPHRINE 12 [hp_X]/29 mL; CORTICOTROPIN 12 [hp_X]/29 mL; HYACINTHOIDES NON-SCRIPTA 12 [hp_X]/29 mL; ONION 12 [hp_X]/29 mL; COLLINSONIA CANADENSIS ROOT 12 [hp_X]/29 mL; CORTISONE ACETATE 12 [hp_X]/29 mL; EUPHRASIA STRICTA 12 [hp_X]/29 mL; GALPHIMIA GLAUCA FLOWERING TOP 12 [hp_X]/29 mL; HISTAMINE DIHYDROCHLORIDE 12 [hp_X]/29 mL; POTASSIUM CHLORIDE 12 [hp_X]/29 mL; SUS SCROFA NASAL MUCOSA 12 [hp_X]/29 mL; SODIUM CHLORIDE 12 [hp_X]/29 mL; SACCHAROMYCES CEREVISIAE RNA 12 [hp_X]/29 mL; RUMEX CRISPUS ROOT 12 [hp_X]/29 mL; SCHOENOCAULON OFFICINALE SEED 12 [hp_X]/29 mL; SAGE 12 [hp_X]/29 mL; TANACETUM VULGARE TOP 12 [hp_X]/29 mL; TRIFOLIUM PRATENSE FLOWER 12 [hp_X]/29 mL; VINCA MINOR 12 [hp_X]/29 mL
INACTIVE INGREDIENTS: CITRIC ACID MONOHYDRATE; POTASSIUM SORBATE; WATER

Allergies Northeaster US

DOSAGE AND ADMINISTRATION

Directions: Before initial dose depress pump 4-5 times or until primed and spray 1 dose directly in mouth 2 to 6 times daily until symptoms improve.

Adult Dose: 3 Pump Sprays

Child's Dose (2-12): 2 Pump Sprays

WARNINGS

Warnings: If symptoms persist or worsen, seek advice of a physician. If pregnant or breast-feeding, take only on advice of physician.

Keep out of reach of children.

Other information: Tamper resistant for your protection. Use only if safety seal is intact.

PURPOSE

Indications: For temporary relief of: •red, itchy, watery eyes •sore throat, cough

From allergies found in: CT. DC. DE. MA. MD. ME. NH. NJ. NY. PA. RI. VT.

ACTIVE INGREDIENT

Active Ingredients: Adenosinum cyclophosphoricum, Adren alinum, Adrenocorticotrophin, Agraphis nutans, Allium cepa, Collinsonia canadensis, Cortisone aceticum, Euphrasia officinlis, Galphimia glauca, Histaminum hydrochloricum, Kali muriaticum, Mucosa nasalis suis, Natrum muriaticum, RNA, Rumex crispus, Sabadilla, Salvia officinalis, Tanacetum vulgare, Trifolium pratense, Vinca minor. Equal volumes of each ingredient in 12X, 30X, LM1 potencies.

Inactive Ingredient: Citric acid, potassium sorbate, purified water.

Indications: For temporary relief of:

- red, itchy, watery eyes
- sore throat, cough

From allergies found in: CT. DC. DE. MA. MD. ME. NH. NJ. NY. PA. RI. VT.